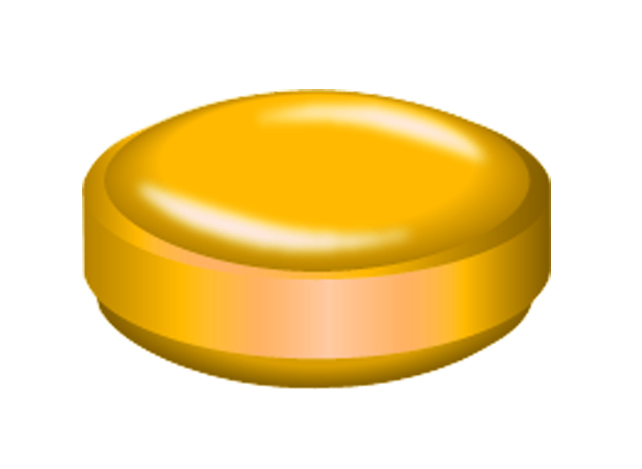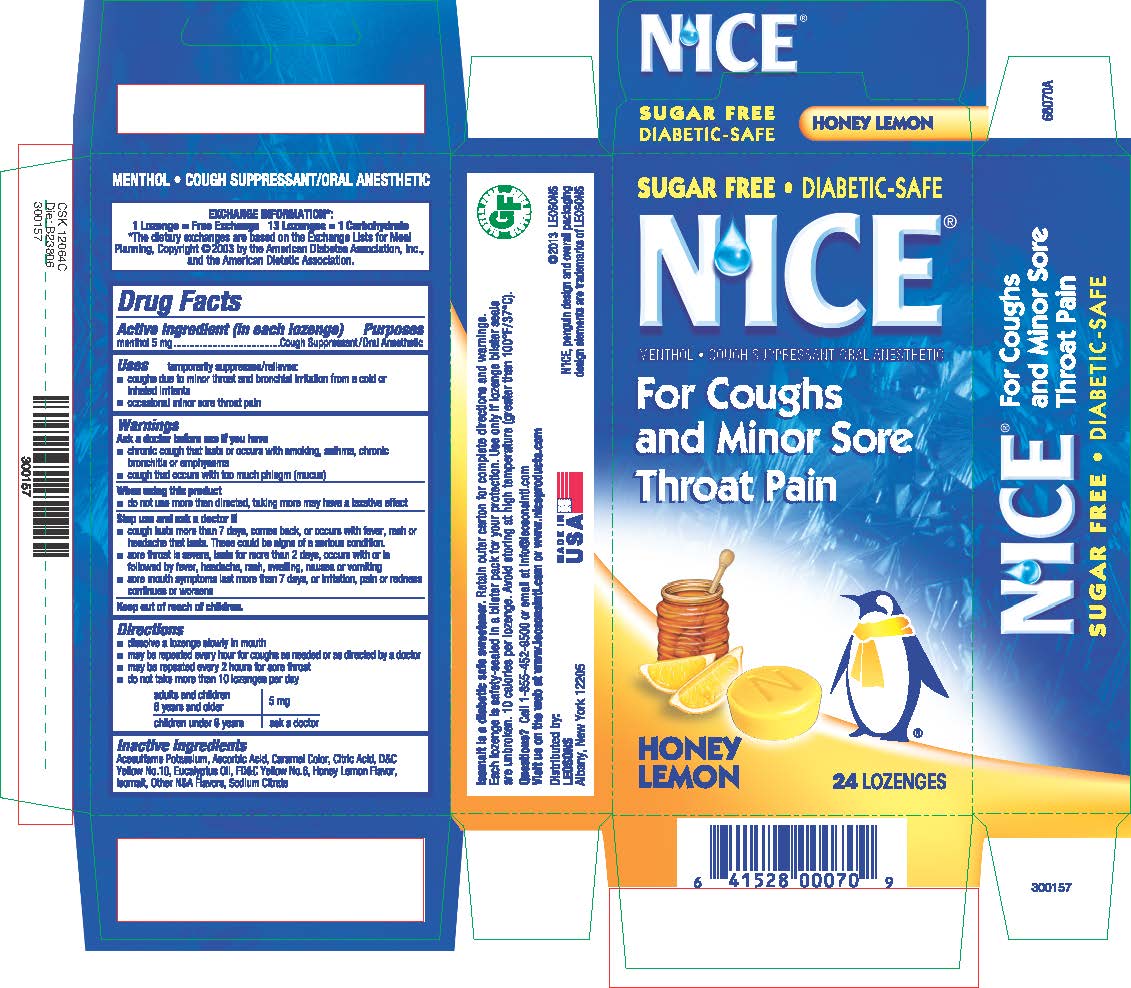 DRUG LABEL: NICE Honey Lemon Cough Drops
NDC: 69626-0045 | Form: LOZENGE
Manufacturer: Leosons Overseas Corp
Category: otc | Type: HUMAN OTC DRUG LABEL
Date: 20241119

ACTIVE INGREDIENTS: MENTHOL 5 mg/1 1
INACTIVE INGREDIENTS: ANHYDROUS CITRIC ACID; EUCALYPTUS OIL; SODIUM CITRATE; ACESULFAME POTASSIUM; ASCORBIC ACID; CARAMEL; D&C YELLOW NO. 10; FD&C YELLOW NO. 6; ISOMALT

Nice Honey Lemon Cough Drops (Best)

Active Ingredient & Purposes

Active Ingredient (in each lozenge) | Purposes
Menthol 5 mg ...... | Cough Suppressant / Oral Anesthetic

Uses

temporarily suppresses / relieves:

- coughs due to minor throat and bronchial irritation from a cold or inhaled irritants
- occasional minor sore throat pain

Warnings

Ask a doctor before use if you have

- chronic cough that lasts or occurs with smoking, asthma, chronic bronchitis or emphysema
- cough that occurs with too much phlegm (mucus)

Ask a doctor before use if you have

- chronic cough that lasts or occurs with smoking, asthma, chronic bronchitis or emphysema
- cough that occurs with too much phlegm (mucus)

When using this product

- do not use more than directed, taking more may have a laxative effect

Stop use and ask doctor if

- cough lasts more than 7 days, comes back, or occurs with fever, rash or headache that lasts. These could be signs of a serious condition.
- sore throat is severe, lasts for more than 2 days, occurs with or is followed by fever, headache, rash, swelling, nausea or vomiting
- sore mouth symptoms last more than 7 days, or irritation, pain or redness continues or worsens

Keep out of reach of children.

Directions

- dissolve a lozenge slowly in mouth
- may be repeated every hour for coughs as needed or as directed by a doctor
- may be repeated every 2 hours for sore throat
- do not take more than 10 lozenges per day

adults and children 6 years and older | 5 mg
children under 6 years | ask a doctor

Inactive Ingredients

Acesulfame Potassium, Ascorbic Acid, Caramel Color, CItric Acid, D&C Yellow No. 10, Eucalyptus Oil, FD&C Yellow No. 6, Honey Lemon Flavor, Isomalt, Other Natural and Artificial Flavors, Sodium Citrate

Questions?

Call 1-855-452-9500 or email at Info@leosonsintl.com